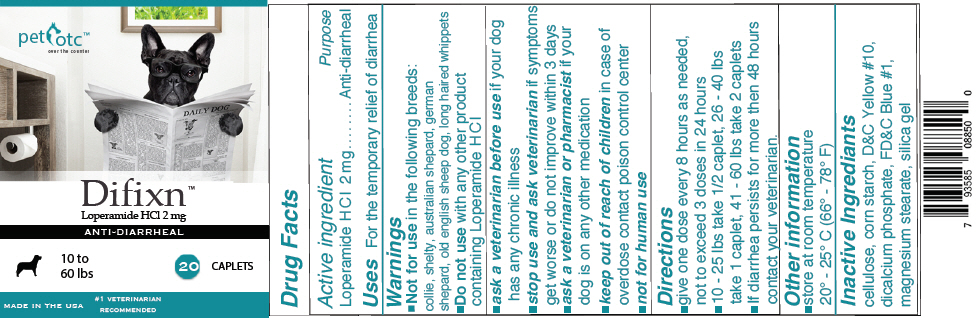 DRUG LABEL: Difixn
NDC: 72087-013 | Form: TABLET
Manufacturer: Goldman Pharmaceutical Group Inc
Category: animal | Type: OTC ANIMAL DRUG LABEL
Date: 20190422

ACTIVE INGREDIENTS: LOPERAMIDE HYDROCHLORIDE 2 mg/1 1
INACTIVE INGREDIENTS: STARCH, CORN; DIBASIC CALCIUM PHOSPHATE DIHYDRATE; MAGNESIUM STEARATE; MICROCRYSTALLINE CELLULOSE; SILICON DIOXIDE

Difixn™

Drug Facts

Active ingredient | Purpose
Loperamide HCl 2 mg | Anti-diarrheal

VETERINARY INDICATIONS

Uses For the temporary relief of diarrhea

Warnings

- Not for use in the following breeds:
  collie, shelty, australian shepard, german shepard, old english sheep dog, long haired whippets
- Do not use with any other product containing Loperamide HCl
- ask a veterinarian before use if your dog has any chronic illness
- stop use and ask veterinarian if symptoms get worse or do not improve within 3 days
- ask a veterinarian or pharmacist if your dog is on any other medication
- keep out of reach of children in case of overdose contact poison control center
- not for human use

Directions

- give one dose every 8 hours as needed, not to exceed 3 doses in 24 hours
- 10 - 25 lbs take 1/2 caplet, 26 - 40 lbs take 1 caplet, 41 - 60 lbs take 2 caplets
- If diarrhea persists for more then 48 hours contact your veterinarian

Other information

- store at room temperature
  20° - 25° (66° - 78° F)

Inactive Ingredients

cellulose, corn starch, D&C Yellow #10, dicalcium phosphate, FD&C Blue #1, magnesium stearate, silica gel

PRINCIPAL DISPLAY PANEL - 2 mg Caplet Bottle Label

pet
otc™
over the counter

Difixn™
Loperamide HCl 2 mg

ANTI-DIARRHEAL

10 to
60 lbs

20 CAPLETS

MADE IN THE USA

#1 VETERINARIAN
RECOMMENDED